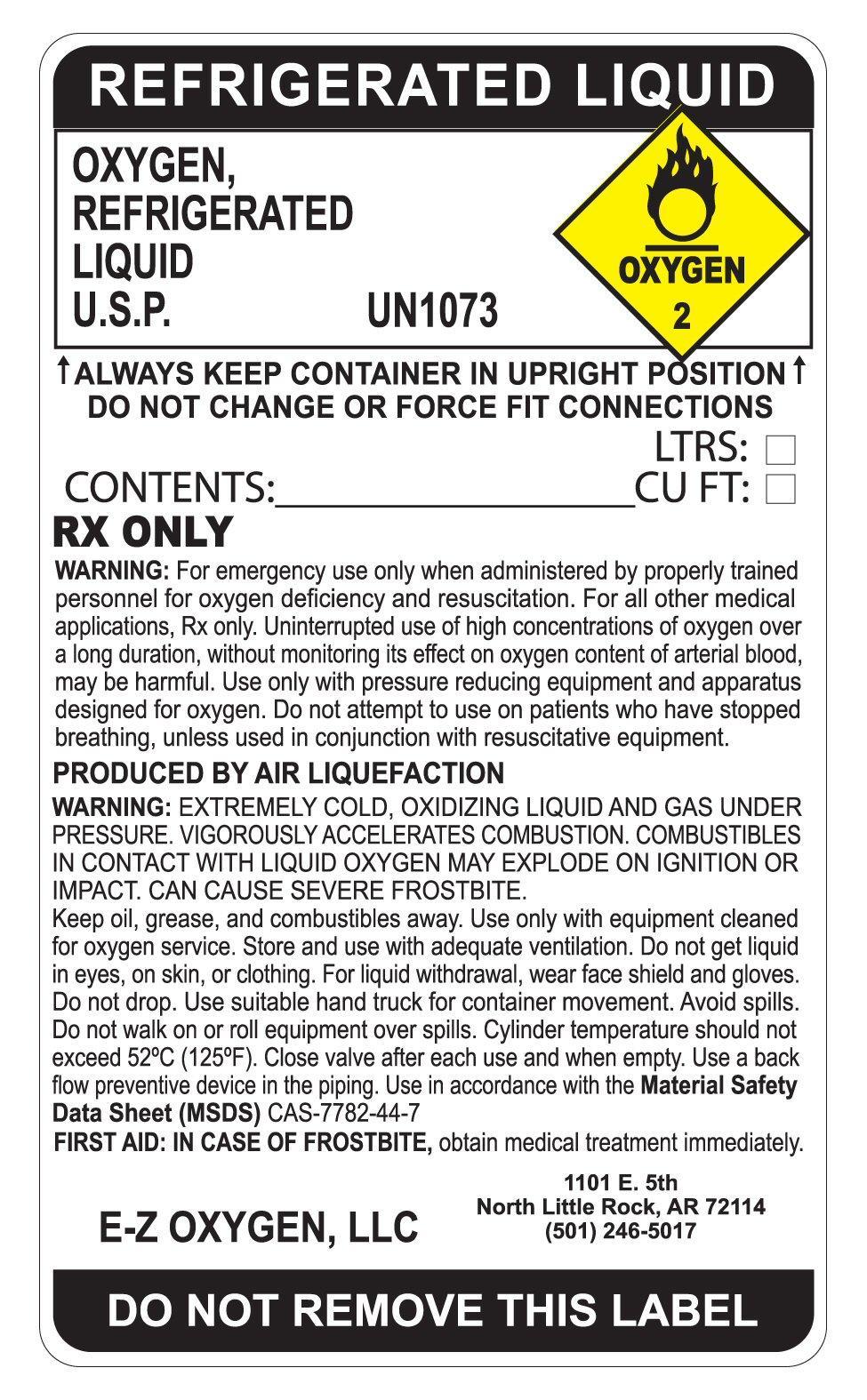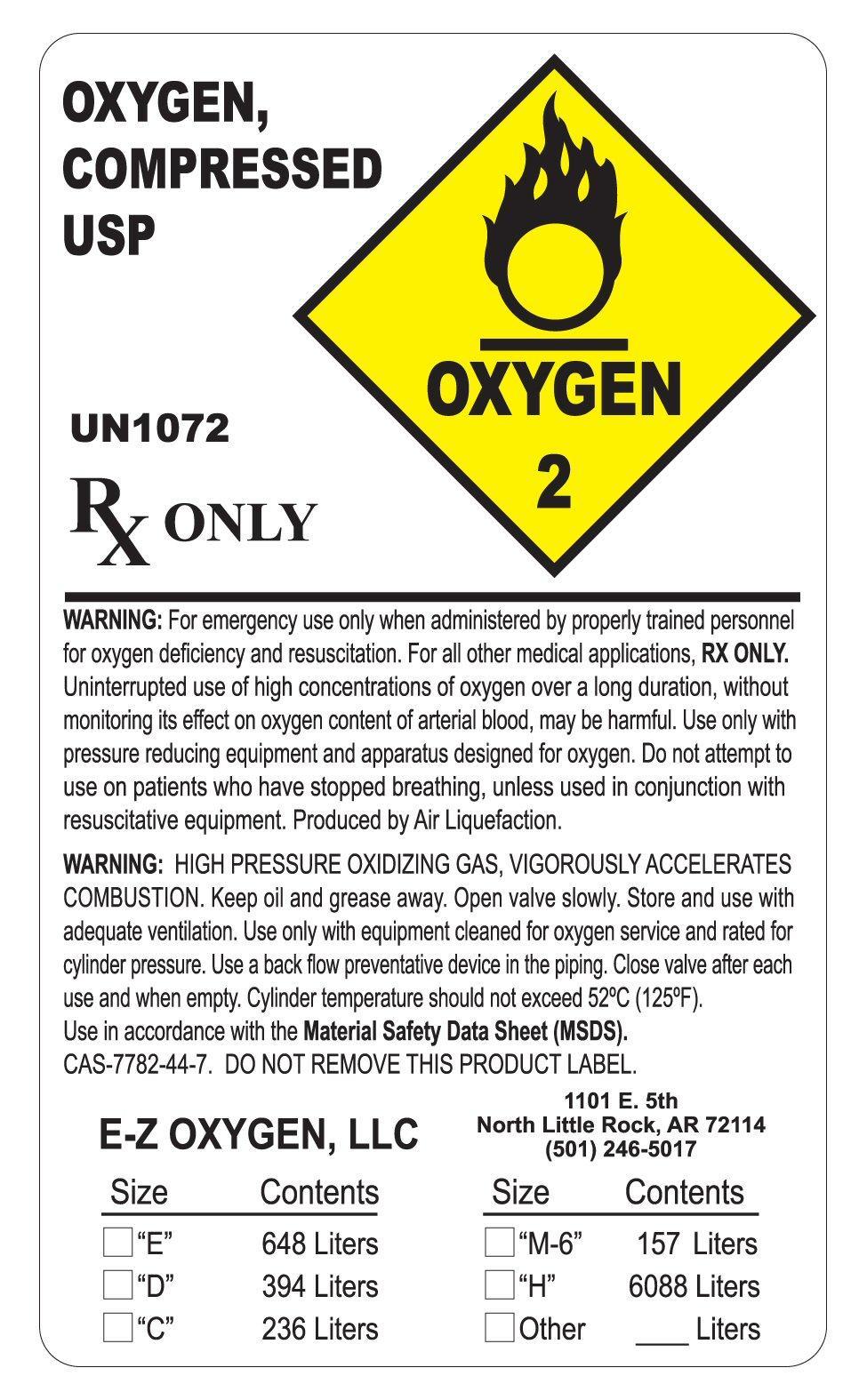 DRUG LABEL: OXYGEN
NDC: 55151-123 | Form: GAS
Manufacturer: E-Z Oxygen LLC, dba AO2
Category: prescription | Type: HUMAN PRESCRIPTION DRUG LABEL
Date: 20251121

ACTIVE INGREDIENTS: OXYGEN 99 L/100 L

OXYGEN HP LABEL

OXYGEN COMPRESSED USP UN1072 OXYGEN 2 RX ONLY

WARNING: FOR EMERGENCY USE ONLY WHEN ADMINISTERED BY PROPERLY TRAINED PERSONNEL FOR OXYGEN DEFICIENCY AND RESUSCITATION. FOR ALL OTHER MEDICAL APPLICATIONS Rx ONLY. UNINTERRUPTED USE OF HIGH CONCENTRATIONS OF OXYGEN OVER A LONG DURATION WITHOUT MONITORING ITS EFFECT ON OXYGEN CONTENT OF ARTERIAL BLOOD, MAY BE HARMFUL. USE ONLY WITH PRESSURE REDUCING EQUIPMENT AND APPARATUS DESIGNED FOR OXYGEN. DO NOT ATTEMPT TO USE ON PATIENTS WHO HAVE STOPPED BREATHING, UNLESS USED IN CONJUNCTION WITH RESUSCITATIVE EQUIPMENT. PRODUCED BY AIR LIQUEFACTION

WARNING: HIGH PRESSURE OXIDIZING GAS, VIGOROUSLY ACCELERATES COMBUSTION. KEEP OIL AND GREASE AWAY. OPEN VALVE SLOWLY. STORE AND USE WITH ADEQUATE VENTILATION. USE ONLY WITH EQUIPMENT CLEANED FOR OXYGEN SERVICE AND RATED FOR CYLINDER PRESSURE. USE A BACK FLOW PREVENTATIVE DEVICE IN THE PIPING. CLOSE VALVE AFTER EACH USE AND WHEN EMPTY. CYLINDER TEMPERATURE SHOULD NOT EXCEED 52 DEGREES C (125 DEGREES F) USE IN ACCORDANCE WITH THE MATERIAL SAFETY DATA SHEET (MSDS) CAS-7782-44-7.DO NOT REMOVE THIS PRODUCT LABEL.
E-Z OXYGEN, LLC 1101 E. 5TH NORTH LITTLE ROCK, AR 72114 (501) 246-5017

SIZE CONTENTS SIZE CONTENTS

"E" 648 LITERS "M-6" 157 LITERS

"D" 394 LITERS "H" 6088 LITERS

"C" 236 LITERS

rres

OXYGEN REFRIGERATED LIQUID LABEL

REFRIGERATED LIQUID OXYGEN REFRIGERATED LIQUID U.S.P. UN1073 OXYGEN 2

ALWAYS KEEP CONTAINER IN UPRIGHT POSITION. DO NOT CHANGE OR FORCE FIT CONNECTIONS.

CONTENTS:_________ LITERS: ___________CU FT: RX ONLY

WARNING: FOR EMERGENCY USE ONLY WHEN ADMINISTERED BY PROPERLY TRAINED PERSONNEL FOR OXYGEN DEFICIENCY AND RESUSCITATION. FOR ALL OTHER MEDICAL APPLICATIONS Rx ONLY. UNINTERRUPTED USE OF HIGH CONCENTRATIONS OF OXYGEN OVER A LONG DURATION, WITHOUT MONITORING ITS EFFECT ON OXYGEN CONTENT OF ARTERIAL BLOOD, MAY BE HARMFUL. USE ONLY WITH PRESSURE REDUCING EQUIPMENT AND APPARATUS DESIGNED FOR OXYGEN. DO NOT ATTEMPT TO USE ON PATIENTS WHO HAVE STOPPED BREATHING, UNLESS USED IN CONJUNCTION WITH RESUSCITATIVE EQUIPMENT. PRODUCED BY AIR LIQUEFACTION.

WARNING: EXTREMELY COLD, OXIDIZING LIQUID AND GAS UNDER PRESSURE. VIGOROUSLY ACCELERATES COMBUSTION. COMBUSTIBLES IN CONTACT WITH LIQUID OXYGEN MAY EXPLODE ON IGNITION OR IMPACT. CAN CAUSE SEVERE FROSTBITE.

KEEP OIL, GREASE, AND COMBUSTIBLES AWAY. USE ONLY WITH EQUIPMENT CLEANED FOR OXYGEN SERVICE. STORE AND USE WITH ADEQUATE VENTILATION. DO NOT GET LIQUID IN EYES, ON SKIN OR CLOTHING. FOR LIQUID WITHDRAWAL, WEAR FACE SHIELD AND GLOVES. DO NOT DROP. USE SUITABLE HAND TRUCK FOR CONTAINER MOVEMENT. AVOID SPILLS. DO NOT WALK OR ROLL EQUIPMENT OVER SPILLS CYLINDER TEMPERATURE SHOULD NOT EXCEED 52 DEGREES C (125 DEGREES F) CLOSE VALVE AFTER EACH USE AND WHEN EMPTY. USE A BACK FLOW PREVENTATIVE DEVICE IN THE PIPING. USE IN ACCORDANCE WITH THE MATERIAL SAFETY DATA SHEET (MSDS) CAS-7782-44-7
FIRST AID: IN CASE OF FROSTBITE OBTAIN MEDICAL TREATMENT IMMEDIATELY.

E-Z OXYGEN, LLC 1101 E. 5TH NORTH LITTLE ROCK, AR 72114 (501) 246-5017

DO NOT REMOVE THIS LABEL

res